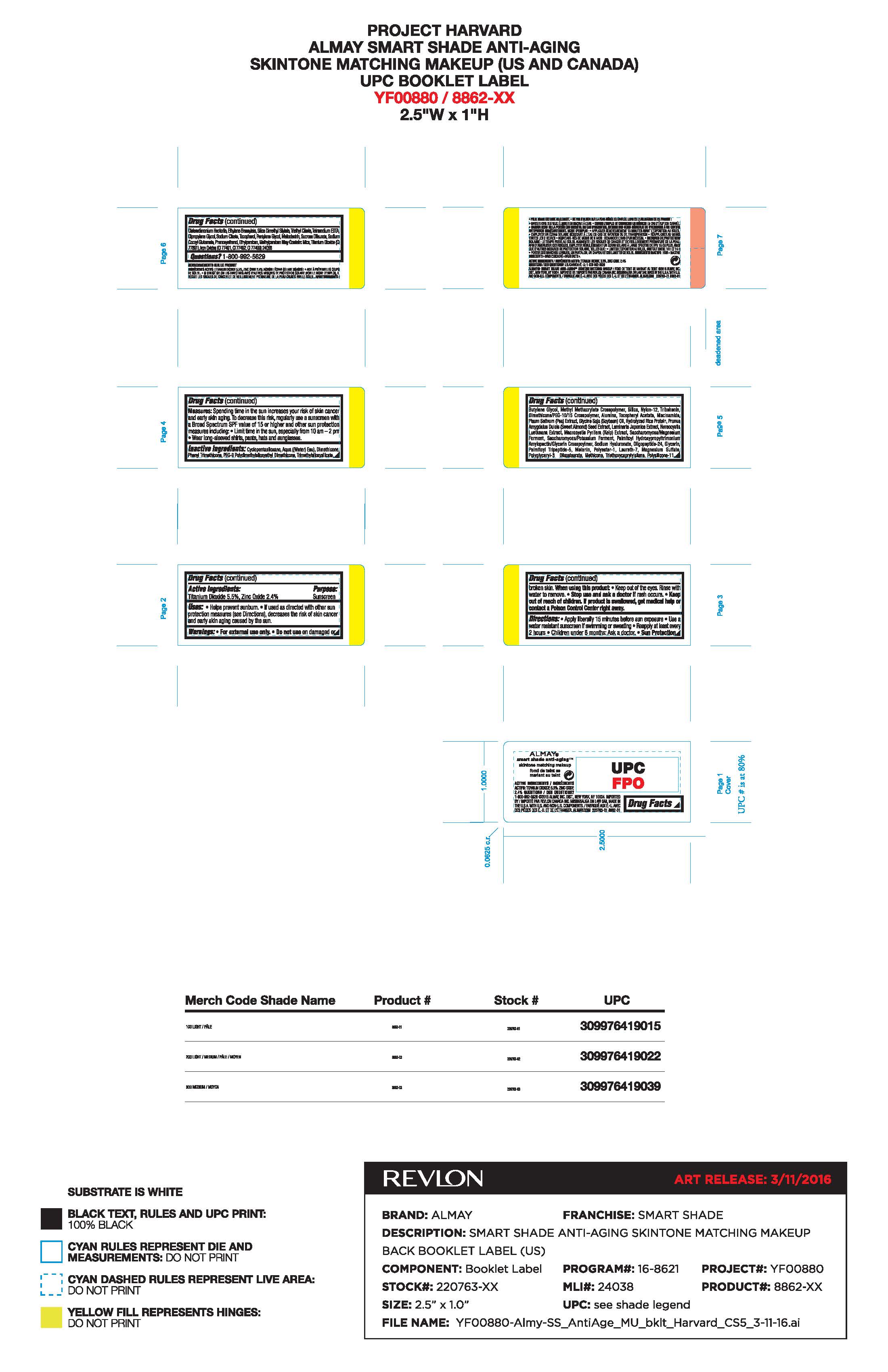 DRUG LABEL: ALMAY SMART SHADE ANTI-AGING SKINTONE MATCHING MAKEUP SPF 20
NDC: 0311-0749 | Form: LIQUID
Manufacturer: Almay, Inc.
Category: otc | Type: HUMAN OTC DRUG LABEL
Date: 20241231

ACTIVE INGREDIENTS: ZINC OXIDE 2.4 mg/1 mL; TITANIUM DIOXIDE 5.5 mg/1 mL
INACTIVE INGREDIENTS: METHICONE (20 CST); MACROCYSTIS PYRIFERA (KELP); ETHYLHEXYLGLYCERIN; DIMETHICONE/PEG-10/15 CROSSPOLYMER; CAPRYLYL GLYCOL; HYDROLYZED RICE PROTEIN (ENZYMATIC; 2000 MW); WATER; PHENYL TRIMETHICONE; GLYCERIN; ALUMINUM OXIDE; HYALURONATE SODIUM; DIMETHICONE; BUTYLENE GLYCOL; NYLON-12; PEG-9 POLYDIMETHYLSILOXYETHYL DIMETHICONE; TRIMETHYLSILOXYSILICATE (M/Q 0.8-1.0); SILICON DIOXIDE; TRIBEHENIN; .ALPHA.-TOCOPHEROL ACETATE; NIACINAMIDE; PEA; SOYBEAN; ALMOND; PALMITOYL TRIPEPTIDE-5; MELANIN SYNTHETIC (TYROSINE, PEROXIDE); LAURETH-7; HYDROGEN DIMETHICONE (13 CST); MAGNESIUM SULFATE, UNSPECIFIED FORM; CYCLOPENTASILOXANE; FERRIC OXIDE RED; POLYGLYCERYL-3 DIISOSTEARATE; TRIETHOXYCAPRYLYLSILANE; DISTEARDIMONIUM HECTORITE; ETHYLENE BRASSYLATE; TRIETHYL CITRATE; SILICA DIMETHYL SILYLATE; TETRASODIUM EDTA; DIPROPYLENE GLYCOL; SODIUM CITRATE; TOCOPHEROL; PENTYLENE GLYCOL; MALTODEXTRIN; SUCROSE DILAURATE; SODIUM COCOYL GLUTAMATE; PHENOXYETHANOL; ETHYLPARABEN; METHYLPARABEN; LAMINARIA JAPONICA; NEREOCYSTIS LUETKEANA; HYDROGENATED SOYBEAN LECITHIN; METHYL METHACRYLATE; FERRIC OXIDE YELLOW; SODIUM OLEATE; MICA; EDETATE DISODIUM; PALMITOYL HYDROXYPROPYLTRIMONIUM AMYLOPECTIN/GLYCERIN CROSSPOLYMER; SACCHAROMYCES CEREVISIAE; FERROSOFERRIC OXIDE; 1,2-HEXANEDIOL

ALMAY SMART SHADE ANTI-AGING SKINTONE MATCHING MAKEUP SPF 20 - Light Medium

Active Ingredients:

Titanium Dioxide: 5.5%

Zinc Oxide 2.4%

Purpose

Sunscreen

Uses:

•Helps prevent sunburn
•If used as directed with other sun protection measures (see Directions), decreases the risk of skin cancer and early skin aging caused by the sun

Warnings:

•For external use only
•Do notuse on damaged or broken skin
•When using this product: Keep out of eyes. Rinse with water to remove.
•Stop use and ask a doctor if a rash occurs
•Keep out of reach of children. If product is swallowed, get medical help or contact a Poison Control center right away

Directions

•Apply liberally 15 minutes before sun exposure
•Use a water resistant sunscreen if swimming or sweating
•Reapply at least every 2 hours
•Children under 6 months: Ask a doctor.

Sun Protection Measures

Spending time in the sun increases your risk of skin cancer and early skin aging. To decrease this risk, regularly use a sunscreen with a Broad Spectrum SPF value of 15 or higher and other sun protection measures including:
•Limit time in the sun, especially from 10 am - 2 pm
•Wear long-sleeved shirts, pants, hats and sunglasses.

Inactive Ingredients

CYCLOPENTASILOXANE, AQUA ((WATER) EAU), DIMETHICONE, PHENYL TRIMETHICONE, PEG-9 POLYDIMETHYLSILOXYETHYL DIMETHICONE, TRIMETHYLSILOXYSILICATE, BUTYLENE GLYCOL, METHYL METHACRYLATE CROSSPOLYMER, SILICA, NYLON-12, TRIBEHENIN, DIMETHICONE/PEG-10/15 CROSSPOLYMER, ALUMINA, TOCOPHERYL ACETATE, NIACINAMIDE, PISUM SATIVUM (PEA) EXTRACT, GLYCINE SOJA (SOYBEAN) OIL, HYDROLYZED RICE PROTEIN, PRUNUS AMYGDALUS DULCIS (SWEET ALMOND) SEED EXTRACT, LAMINARIA JAPONICA EXTRACT, NEREOCYSTIS LUETKEANA EXTRACT, MACROCYSTIS PYRIFERA (KELP) EXTRACT, SACCHAROMYCES/MAGNESIUM FERMENT, SACCHAROMYCES/POTASSIUM FERMENT, PALMITOYL HYDROXYPROPYLTRIMONIUM AMYLOPECTIN/GLYCERIN CROSSPOLYMER, SODIUM HYALURONATE, OLIGOPEPTIDE-24, GLYCERIN, PALMITOYL TRIPEPTIDE-5, MELANIN, POLYESTER-1, LAURETH-7, MAGNESIUM SULFATE, POLYGLYCERYL-3 DIISOSTEARATE, METHICONE, TRIETHOXYCAPRYLYLSILANE, POLYSILICONE-11, DISTEARDIMONIUM HECTORITE, ETHYLENE BRASSYLATE, SILICA DIMETHYL SILYLATE, TRIETHYL CITRATE, TETRASODIUM EDTA, DIPROPYLENE GLYCOL, SODIUM CITRATE, TOCOPHEROL, PENTYLENE GLYCOL, MALTODEXTRIN, SUCROSE DILAURATE, SODIUM COCOYL GLUTAMATE, PHENOXYETHANOL, ETHYLPARABEN, METHYLPARABEN

KEEP OUT OF REACH OF CHILDREN

Keep out of the reach of children. If product is swallowed, get medical help or contact a Poison Control Center right away.

DOSAGE AND ADMINISTRATION

Apply liberally 15 minutes before sun exposure.

Principal Display Panel

Almay

ALMAY SMART SHADE ANTI-AGING SKINTONE MATCHING MAKEUP SPF 20

1 oz/ 30mL